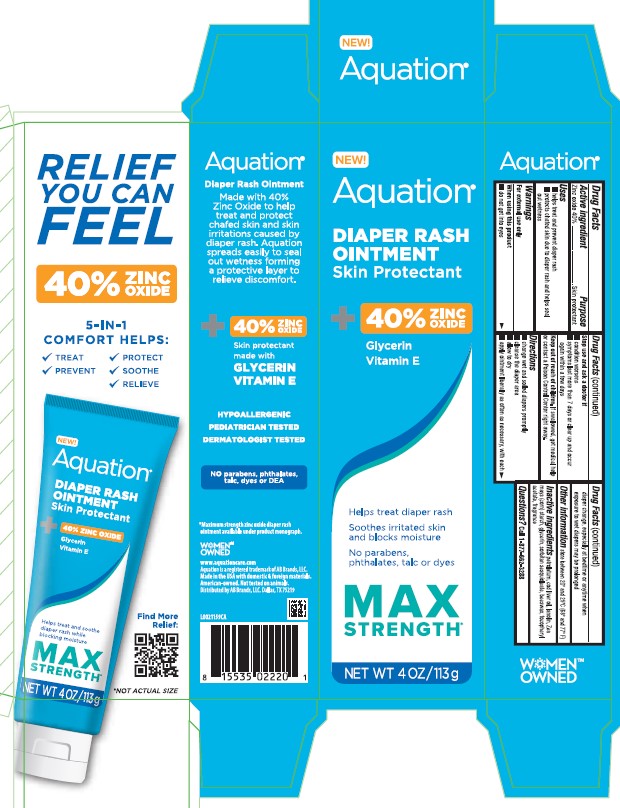 DRUG LABEL: Zinc oxide
NDC: 83514-0020 | Form: OINTMENT
Manufacturer: AB Brands, LLC
Category: otc | Type: HUMAN OTC DRUG LABEL
Date: 20260129

ACTIVE INGREDIENTS: ZINC OXIDE 400 mg/1 g
INACTIVE INGREDIENTS: PETROLATUM; COD LIVER OIL; LANOLIN; STARCH, CORN; GLYCERIN; SORBITAN SESQUIOLEATE; YELLOW WAX; .ALPHA.-TOCOPHEROL ACETATE

Aquation 020.002/020AC-AD
Diaper Rash Ointment 40% Zinc Oxide

Active ingredients

Zinc oxide 40%

Purpose

Skin protectant

Uses

- helps treat and prevent diaper rash
- protects chafed skin due to diaper rash and helps seal out wetness

Warnings

For external use only

When using this product

do not get into eyes

Stop use and ask a doctor if

- condition worsens
- symptoms last more than 7 days or clear up and occur again within a few days

Keep out of reach of children.

If swallowed, get medical help or contact a Poison Control Center right away.

Directions

- change wet and soiled diapers promptly
- cleanse the diaper area
- allow to dry
- apply ointment liberally as often as necessary, with each diaper change, especially at bedtime or anytime when exposure to wet diapers may be prolonged

Other information

store between 20⁰ and 25⁰C (68⁰ and 77⁰F)

Inactive ingredients

petrolatum, cod liver oil, lanolin, Zea mays (corn) starch, glycerin, sorbitan sesquioleate, beeswax, tocopheryl acetate, fragrance

Questions?

Call 1-877-662-3288

Claims - Side panel

RELIEF YOU CAN FEEL

40% ZINC OXIDE

5-IN-1 COMFORT HELPS

- TREAT
- PREVENT
- PROTECT
- SOOTHE
- RELIEVE

Back panel - Claims & Adverse reactions

Aquation ®

Diaper Rash Ointment

Made with 40% Zinc Oxide to help treat and protect chafed skin and skin irritations caused by rash. Aquation spreads easily to seal out wetness forming a protective layer to relieve discomfort.

40% ZINC OXIDE

Skin protectant made with

GLYCERIN

VITAMIN E

HYPOALLERGENIC

PEDIATRICIAN TESTED

DERMATOLOGIST TESTED

No parabens, phthalates, talc, dyes or DEA

*Maximum strength zinc oxide diaper rash ointment available under product monograph.

WOMEN™ OWNED

www.aquationcare.com

Aquation is a registed trademark of AB Brands, LLC.

Made in the USA with domestic & foreign materials.

American-owned. Not tested on animals.

Distributed by AB Brands, LLC Dallas, TX 75219

Principal display panel

NEW!

Aquation®

DIAPER RASH OINTMENT

Skin Protectant

40% ZINC OXIDE

GLYCERIN

VITAMIN E

Helps treat diaper rash

Soothes irritated skin and blocks moisture

No parabens, phthalates, talc or dyes

MAX STRENGTH

NET WT 4 OZ/113 g